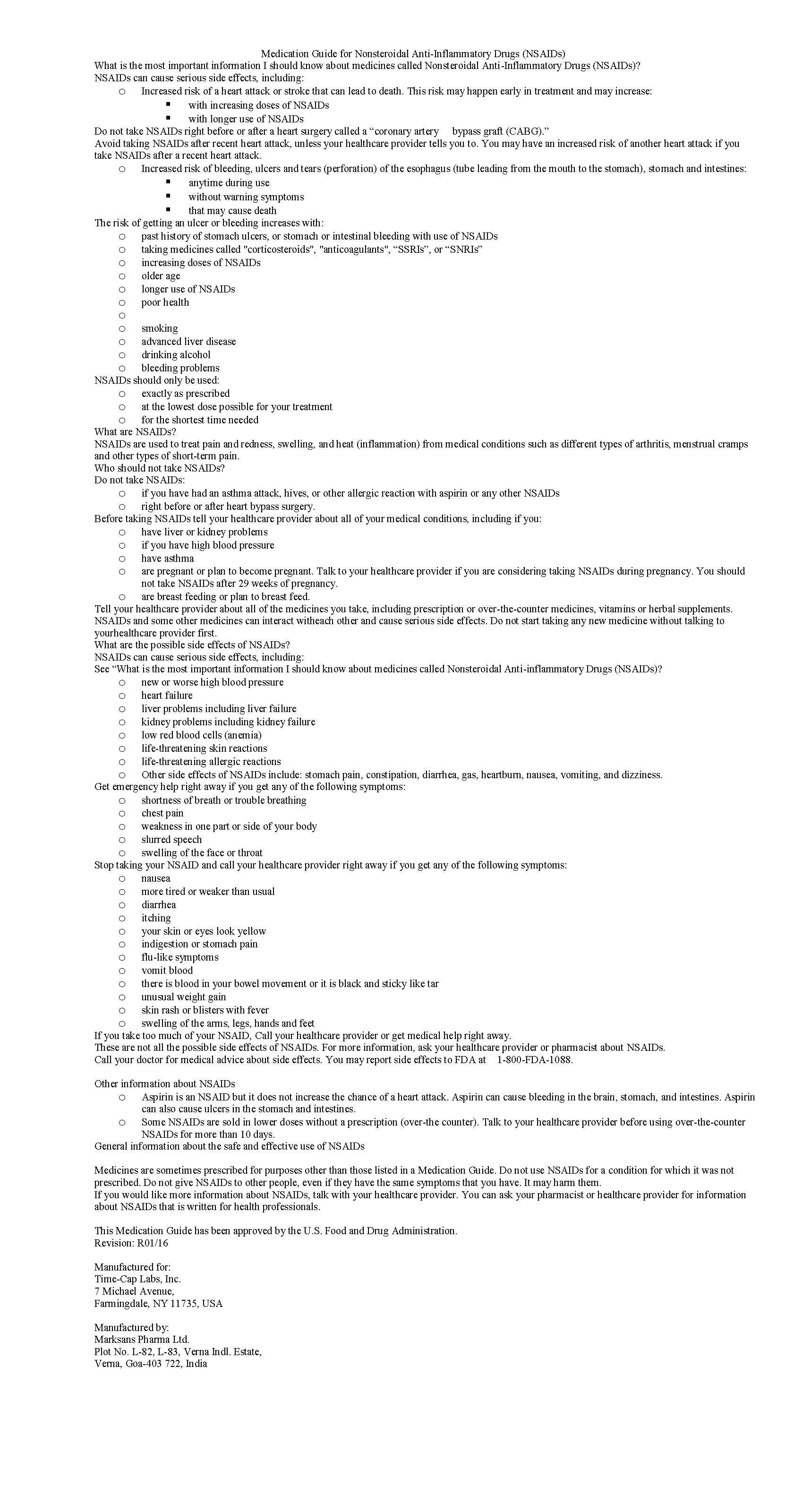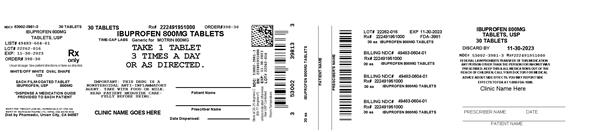 DRUG LABEL: IBUPROFEN
NDC: 53002-3981 | Form: TABLET, FILM COATED
Manufacturer: RPK Pharmaceuticals, Inc.
Category: prescription | Type: HUMAN PRESCRIPTION DRUG LABEL
Date: 20230706

ACTIVE INGREDIENTS: IBUPROFEN 800 mg/1 1
INACTIVE INGREDIENTS: SILICON DIOXIDE; CROSCARMELLOSE SODIUM; MAGNESIUM STEARATE; MICROCRYSTALLINE CELLULOSE; POLYETHYLENE GLYCOL, UNSPECIFIED; POLYVINYL ALCOHOL, UNSPECIFIED; STARCH, CORN; TALC; TITANIUM DIOXIDE

IBUPROFEN 400 MG - 600 MG AND 800 MG TABLETS

HOW SUPPLIED

Product: 53002-3981

NDC: 53002-3981-1 10 TABLET, FILM COATED in a BOTTLE

NDC: 53002-3981-2 15 TABLET, FILM COATED in a BOTTLE

NDC: 53002-3981-3 30 TABLET, FILM COATED in a BOTTLE

NDC: 53002-3981-5 50 TABLET, FILM COATED in a BOTTLE